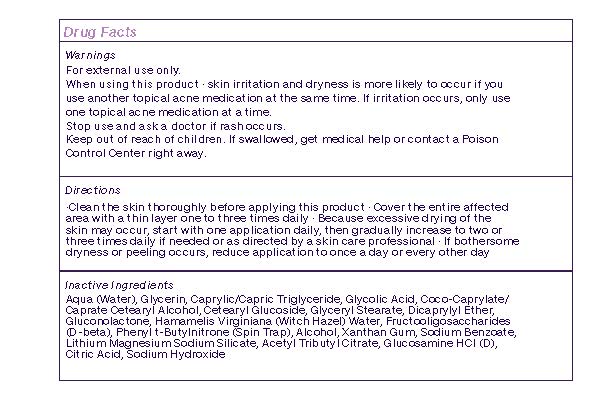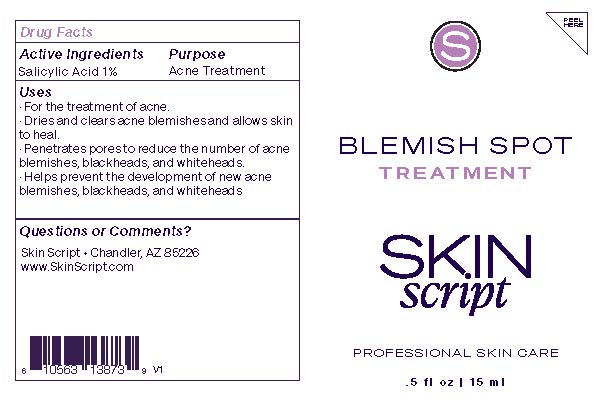 DRUG LABEL: Blemish Spot Treatment
NDC: 83657-472 | Form: CREAM
Manufacturer: Skin Script, LLC
Category: otc | Type: HUMAN OTC DRUG LABEL
Date: 20251229

ACTIVE INGREDIENTS: SALICYLIC ACID 0.01 g/1 g
INACTIVE INGREDIENTS: CETOSTEARYL ALCOHOL; GLYCOLIC ACID; GLUCONOLACTONE; ACETYLTRIBUTYL CITRATE; ALCOHOL; GLYCERIN; COCO-CAPRYLATE/CAPRATE; CETEARYL GLUCOSIDE; LAPONITE; SODIUM BENZOATE; WATER; MEDIUM-CHAIN TRIGLYCERIDES; DICAPRYLYL ETHER; SODIUM HYDROXIDE; GLUCOSAMINE HYDROCHLORIDE; XANTHAN GUM; GLYCERYL MONOSTEARATE; PHENYL-N-TERT-BUTYLNITRONE; HAMAMELIS VIRGINIANA TOP WATER; SACCHARUM OFFICINARUM STEM FRUCTOOLIGOSACCHARIDES; CITRIC ACID

Active Ingredients

Salicylic Acid 1%

Purpose

Acne Treatment

Uses

- For the treatment of acne.
- Dries and clears acne blemishes and allows skin to heal.
- Penetrates pores to reduce the number of acne blemishes, blackheads, and whiteheads.
- Helps prevent the development of new acne blemishes, blackheads, and whiteheads.

Questions or comments?

Skin Script™

Chandler, AZ 85226

www.skinscript.com

Warnings

For external use only

When using this product · skin irritation and dryness is more likely to occur if you use

another topical acne medication at the same time. If irritation occurs, only use one

topical acne medication at a time.

Stop use and ask a doctor if rash occurs.

Keep out of reach of children. If swallowed, get medical help or contact a Poison

Control Center right away.

Keep Out of Reach of Children

Directions

· Clean the skin thoroughly before applying this product · Cover the entire affected area

with a thin layer one to three times daily · Because excessive drying of the skin may

occur, start with one application daily, then gradually increase to two or three times

daily if needed or as directed by a skin care professional · If bothersome dryness or

peeling occurs, reduce application to once a day or every other day

Inactive Ingredients

Inactive Ingredients: Aqua (Water), Glycerin, Caprylic/Capric Triglyceride, Glycolic Acid, Coco-Caprylate/Caprate, Cetearyl Alcohol, Cetearyl Glucoside, Glyceryl Stearate, Dicaprylyl Ether, Gluconolactone, Hamamelis Virginiana (Witch Hazel) Water, Fructooligosaccharides (D-beta), Phenyl t-Butylnitrone (Spin Trap), Alcohol, Xanthan Gum, Sodium Benzoate, Lithium Magnesium Sodium Silicate, Acetyl Tributyl Citrate, Glucosamine HCl (D), Citric Acid, Sodium Hydroxide